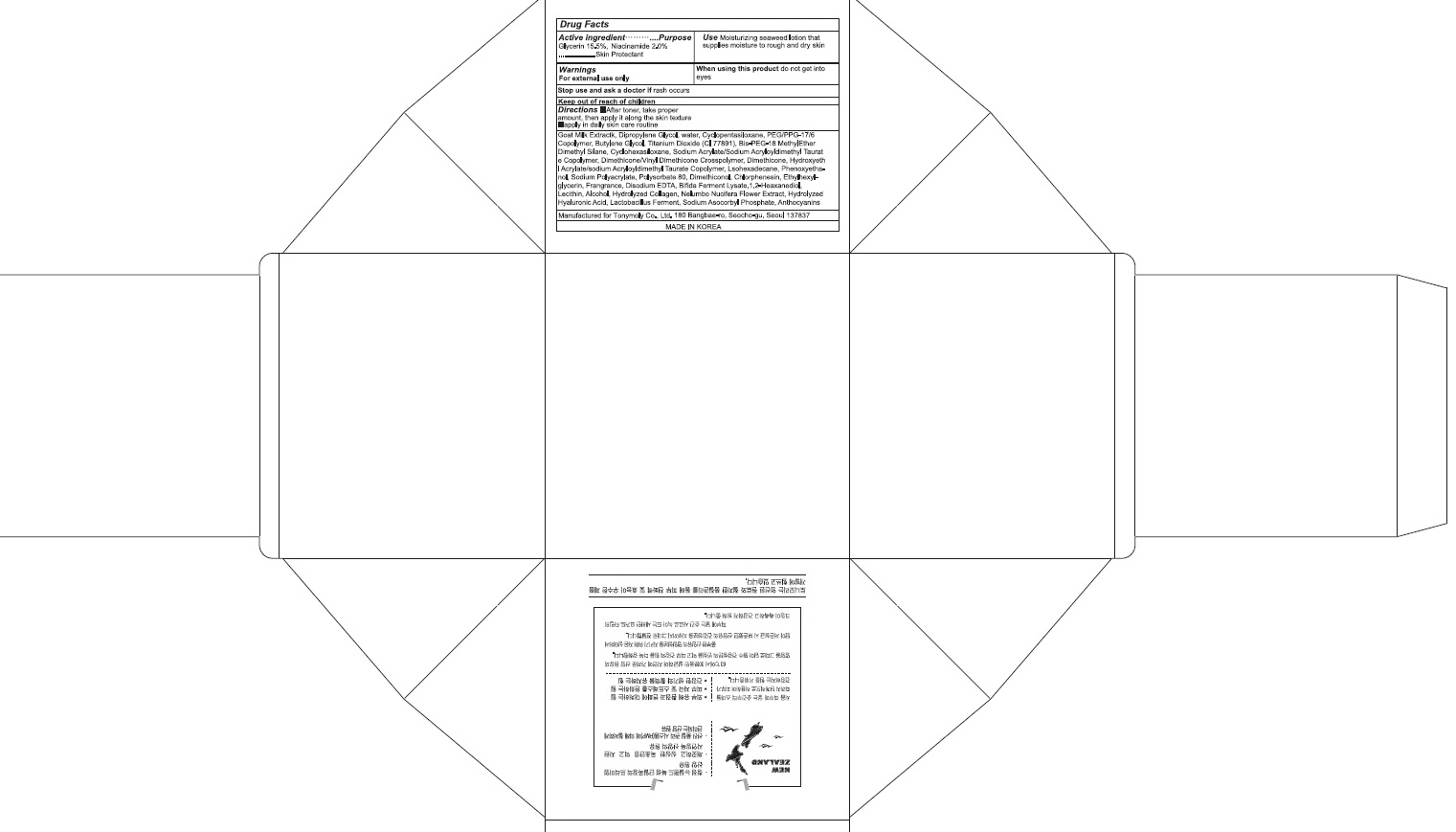 DRUG LABEL: NATURALTH GOAT MILK PREMIUM TONE UP
NDC: 59078-301 | Form: CREAM
Manufacturer: TONYMOLY CO.,LTD
Category: otc | Type: HUMAN OTC DRUG LABEL
Date: 20160527

ACTIVE INGREDIENTS: Glycerin 9.3 g/60 mL; Niacinamide 1.2 g/60 mL
INACTIVE INGREDIENTS: Dipropylene Glycol; Water

ACTIVE INGREDIENT

Active ingredient: Glycerin 15.5%, Niacinamide 2.0%

INACTIVE INGREDIENT

Inactive Ingredient: Goat Milk Extract, Dipropylene Glycol, Water, Cyclopentasiloxane, PEG/PPG-17/6 Copolymer, Butylene Glycol, Titanium Dioxide (CI 77891), Bis-PEG-18 Methyl Ether Dimethyl Silane, Cyclohexasiloxane, Sodium Acrylate/Sodium Acryloyldimethyl Taurate Copolymer, Dimethicone/Vinyl Dimethicone Crosspolymer, Dimethicone, Hydroxyethyl Acrylate/Sodium Acryloyldimethyl Taurate Copolymer, Isohexadecane, Phenoxyethanol, Sodium Polyacrylate, Polysorbate 80, Dimethiconol, Chlorphenesin, Ethylhexylglycerin, Caprylyl Glycol, Triethoxycaprylylsilane, Fragrance, Disodium EDTA, Bifida Ferment Lysate, 1,2-Hexanediol, Lecithin, Alcohol, Hydrolyzed Collagen, Nelumbo Nucifera Flower Extract, Hydrolyzed Hyaluronic Acid, Lactobacillus Ferment, Sodium Ascorbyl Phosphate, Anthocyanins

PURPOSE

Purpose: Skin Protectant

WARNINGS

Warnings: For external use only. When using this product do not get into eyes. Stop use and ask a doctor if rash occurs. Do not use on - deep puncture wounds - animal bites - serious burns Keep out of reach of children.

KEEP OUT OF REACH OF CHILDREN

Use

Use: helps prevent and relieve chapped or cracked skin

Directions

Directions: - After toner, take proper amount, then apply it along the skin texture - apply in daily skin care routine